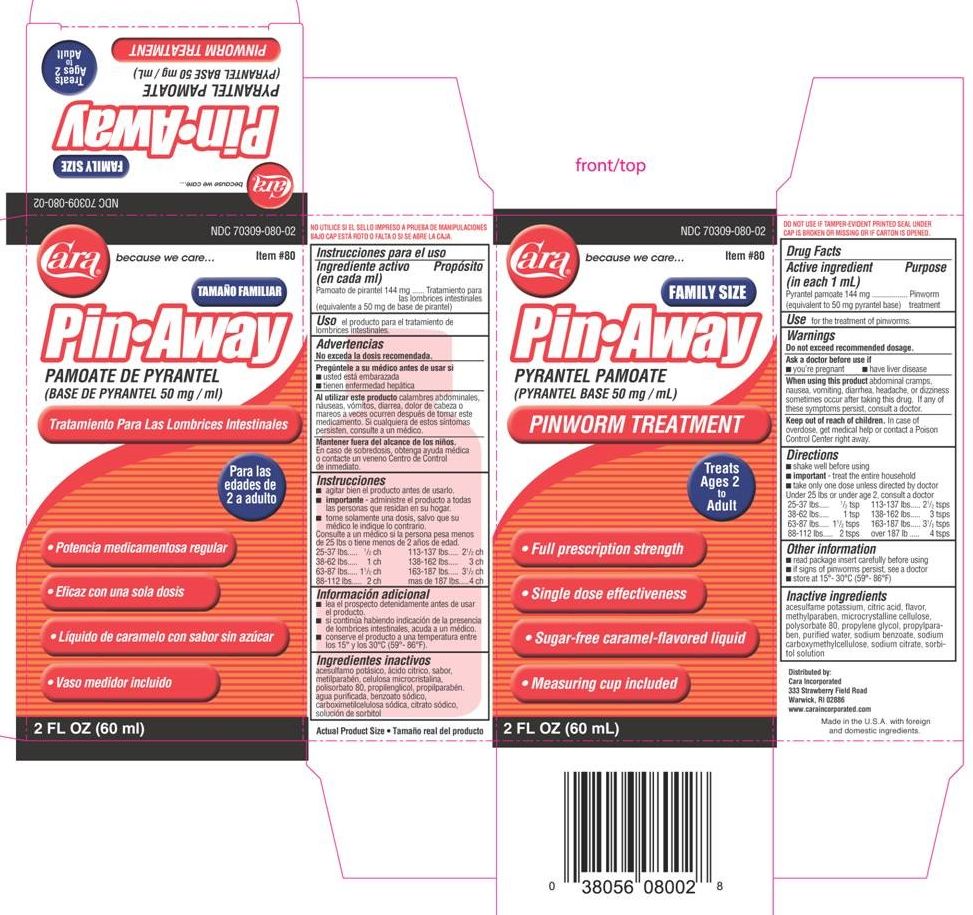 DRUG LABEL: PinAway
NDC: 70309-080 | Form: SUSPENSION
Manufacturer: Cara, Incorporated
Category: otc | Type: HUMAN OTC DRUG LABEL
Date: 20151207

ACTIVE INGREDIENTS: PYRANTEL PAMOATE 144 mg/1 mL
INACTIVE INGREDIENTS: CITRIC ACID MONOHYDRATE; PROPYLPARABEN; WATER; METHYLPARABEN; CARBOXYMETHYLCELLULOSE SODIUM; SODIUM CITRATE; SORBITOL; ACESULFAME POTASSIUM; CELLULOSE, MICROCRYSTALLINE; POLYSORBATE 80; PROPYLENE GLYCOL; SODIUM BENZOATE

PIN-AWAY

Active ingredient (in each 1 mL)

Pyrantel pamoate 144 mg

(equivalent to 50 mg pyrantel base)

Purpose

Pinworm treatment

Use

for the treatment of pinworms.

Warnings

Do not exceed recommended dosage.

Ask a doctor before use if

- you're pregnant
- have liver disease

When using this product abdominal cramps, nausea, vomiting, diarrhea, headache, or dizziness sometimes occur after taking this drug. If any of these symptoms persist, consult a doctor.

Keep out of reach of children. In case of overdose, get medical help or contact a Poison Control Center right away.

Directions

- shake well before using
- important - treat the entire household
- take only one dose unless directed by a doctor

Under 25 lbs or under age 2, consult a doctor

25-37 lbs.......1/2 tsp

38-62 lbs.......1 tsp

63-87 lbs.......1^1/2 tsp

88-112 lbs.....2 tsps

113-137 lbs...2^1/2 tsps

138-162 lbs...3 tsps

163-187 lbs...3^1/2 tsps

over187 lbs....4 tsps

Other information

- read package insert carefully before using
- if signs of pinworm persist, see a doctor

STORAGE AND HANDLING

- store at 15°- 30°C (59°- 86°F)

Inactive ingredients

acesulfame potassium, citric acid, flavor, methylparaben, microcrystalline cellulose, polysorbate 80, propylene glycol, propylparaben, purified water, sodium benzoate, sodium carboxymethylcellulose, sodium citrate, sorbitol solution

Distributed by:

Cara Incorporated

333 Strawberry Field Road

Warwick, RI 02886

www.caraincorporated.com

Made in U.S.A. with foreign and domestic ingredients.

Cara PinAway

NDC 70309-080-02

PYRANTEL PAMOATE

(PYRANTEL BASE 50 mg / mL)

PINWORM TREATMENT

Treats Ages 2 to Adult

- Full prescription strength
- Single dose effectiveness
- Sugar-free caramel-flavored liquid
- Measuring cup included

2 FL OZ (60 mL)